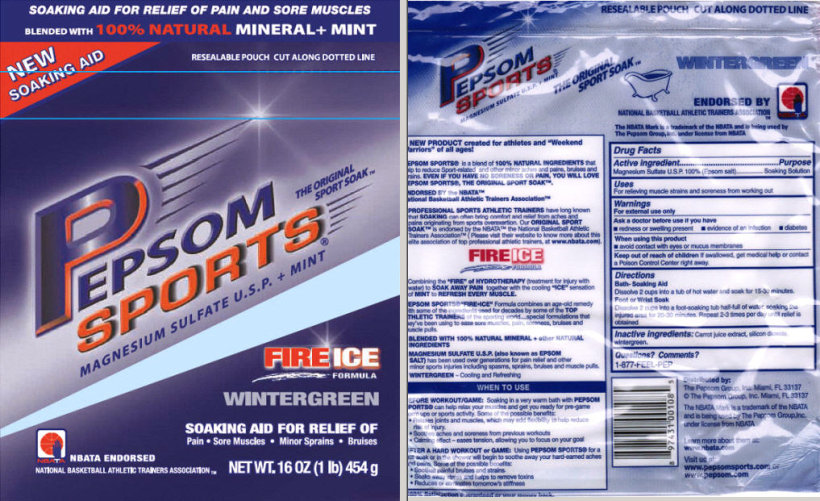 DRUG LABEL: PEPSOM SPORTS WINTERGREEN 
NDC: 51619-300 | Form: FOR SOLUTION
Manufacturer: The Pepsom Group, Inc.
Category: otc | Type: HUMAN OTC DRUG LABEL
Date: 20100527

ACTIVE INGREDIENTS: Magnesium Sulfate, Unspecified 1 kg/1 kg
INACTIVE INGREDIENTS: Silicon Dioxide

Pepsom Sports Magnesium Sulfate U.S.P. + Mint
Drug Facts

Active Ingredient

Magnesium Sulfate U.S.P. 100% (Epsom salt)

Purpose

Soaking Solution

Uses

For relieving muscle strains and soreness from working out

Warnings

For external use only

Ask a doctor before use if you have

- redness or swelling present
- evidence of an infection
- diabetes

When using this product

- avoid contact with eyes or mucus membranes

Keep out of reach of children

If swallowed, get medical help or contact a Poison Control Center right away.

Directions

Bath- Soaking Aid

Dissolve 2 cups into a tub of hot water and soak for 15-30 minutes.

Foot or Wrist Soak

Dissolve 2 cups into a foot-soaking tub half-full of water, soaking the injured area for 20-30 minutes. Repeat 2-3 times per day until relief is obtained.

Inactive ingredients:

Carrot juice extract, silicon dioxide, wintergreen.

Questions? Comments?

1-877-FEEL-PEP

Principal Display Panel

SOAKING AID FOR RELIEF OF PAIN AND SORE MUSCLES

BLENDED WITH 100% NATURAL MINERAL+ MINT

NEW SOAKING AID

RESEALABLE POUCH CUT ALONG DOTTED LINE

PEPSOM SPORTS®

THE ORIGINAL SPORT SOAKTM

MAGNESIUM SULFATE U.S.P. + MINT

FIRE ICE FORMULA

WINTERGREEN

SOAKING AID FOR RELIEF OF
Pain • Sore Muscles • Minor Sprains • Bruises

NBATA ENDORSED
NATIONAL BASKETBALL ATHLETIC TRAINERS ASSOCIATIONTM

NET WT. 16 OZ (1 lb.) 454 g

RESEALABLE POUCH CUT ALONG DOTTED LINE

PEPSOM SPORTS®
MAGNESIUM SULFATE U.S.P. + MINT

THE ORIGINAL SPORT SOAKTM

WINTERGREEN

ENDORSED BY
NATIONAL BASKETBALL ATHLETIC TRAINERS ASSOCIATIONTM

The NBATA Mark is a trademark of the NBATA and is being used by
The Pepsom Group, Inc. under license from NBATA

A NEW PRODUCT created for athletes and "Weekend Warriors" of all ages!

PEPSOM SPORTS® is a blend of 100% NATURAL INGREDIENTS that help to reduce Sport-related and other minor aches and pains, bruises and strains. EVEN IF YOU HAVE NO SORENESS OR PAIN, YOU WILL LOVE PEPSOM SPORTS®, THE ORIGINAL SPORT SOAK™.

ENDORSED BY the NBATA™
National Basketball Athletic Trainers Association™

- PROFESSIONAL SPORTS ATHLETIC TRAINERS have long known that SOAKING can often bring comfort and relief from aches and pains originating from sports overexertion. Our ORIGINAL SPORT SOAK™ is endorsed by the NBATA™ the National Basketball Athletic Trainers Association™ (Please visit their website to know more about this elite association of top professional athletic trainers, at www.nbata.com).

FIRE ICE FORMULA

Combining the "FIRE" of HYDROTHERAPY (treatment for injury with water) to SOAK AWAY PAIN together with the cooling "ICE" sensation of MINT to REFRESH EVERY MUSCLE.

PEPSOM SPORTS® "FIRE★ICE" Formula combines an age-old remedy with some of the ingredients used for decades by some of the TOP ATHLETIC TRAINERS of the sporting world....special formulations that they've been using to ease sore muscles, pain, soreness, bruises and muscle pulls.

- BLENDED WITH 100% NATURAL MINERAL + other NATURAL INGREDIENTS
- MAGNESIUM SULFATE U.S.P. (also known as EPSOM SALT) has been used over generations for pain relief and other minor sports injuries including spasms, sprains, bruises and muscle pulls.
- WINTERGREEN - Cooling and Refreshing

WHEN TO USE

BEFORE WORKOUT/GAME: Soaking in a very warm bath with PEPSOM SPORTS® can help relax your muscles and get you ready for pre-game warm ups or sports activity. Some of the possible benefits:

- Relaxes joints and muscles, which may add flexibility to help reduce risk of injury.
- Soothes aches and soreness from previous workouts
- Calming effect - eases tension, allowing you to focus on your goal

AFTER A HARD WORKOUT or GAME: Using PEPSOM SPORTS® for a hot soak or in the shower will begin to soothe away your hard-earned aches and pains. Some of the possible benefits:

- Soothes painful bruises and strains
- Soaks away stress and helps to remove toxins
- Reduces or eliminates tomorrow's stiffness

100% Satisfaction guaranteed or your money back.

Distributed by:
The Pepsom Group, Inc. Miami, FL 33137
© The Pepsom Group, Inc. Miami, FL 33137

THE NBATA Mark is a trademark of the NBATA and is being used by The Pepcom Group, Inc. under license from NBATA

Learn more about them at:
www.nbata.com

Visit us at:
www.pepsomsports.com or
www.pepsom.com